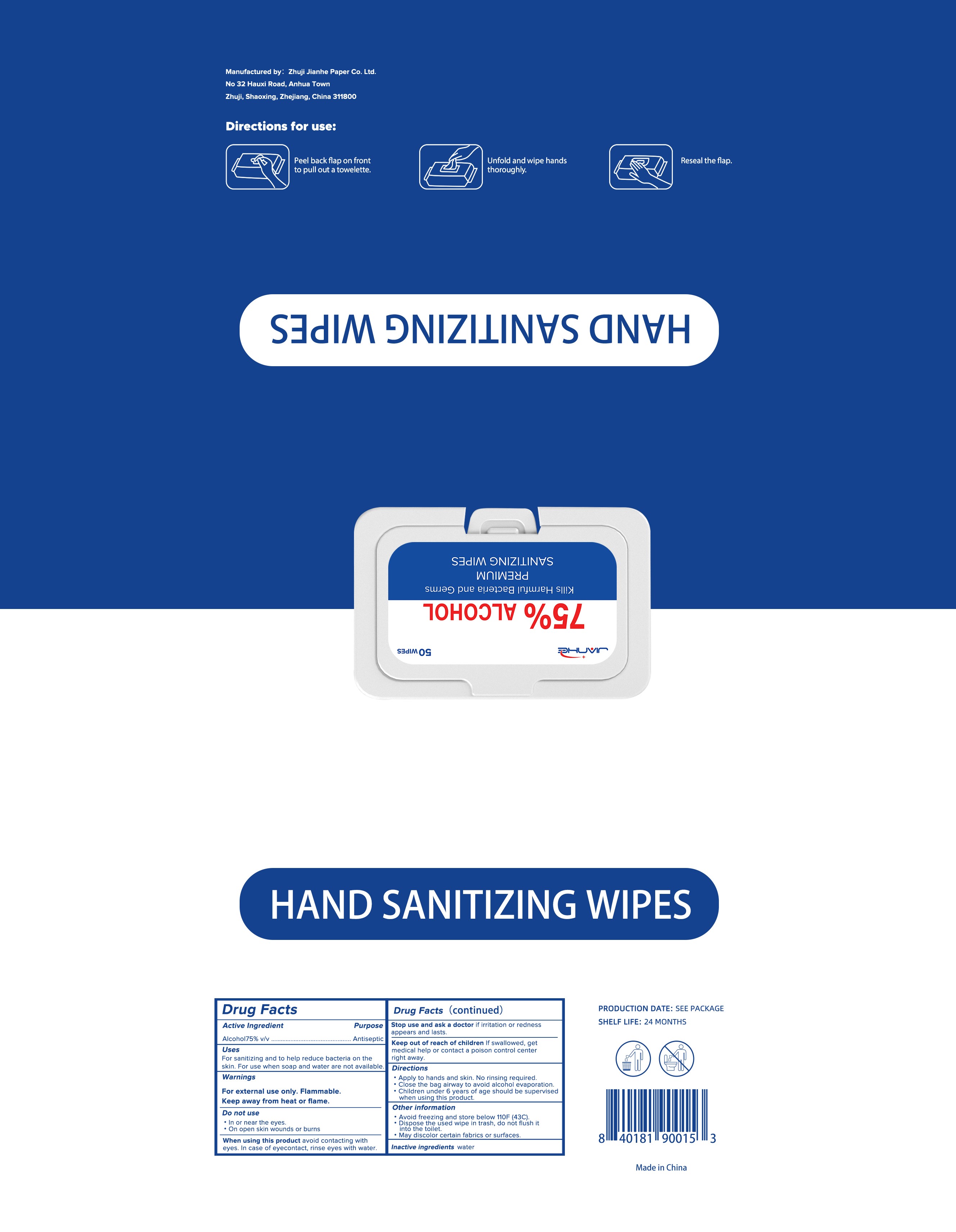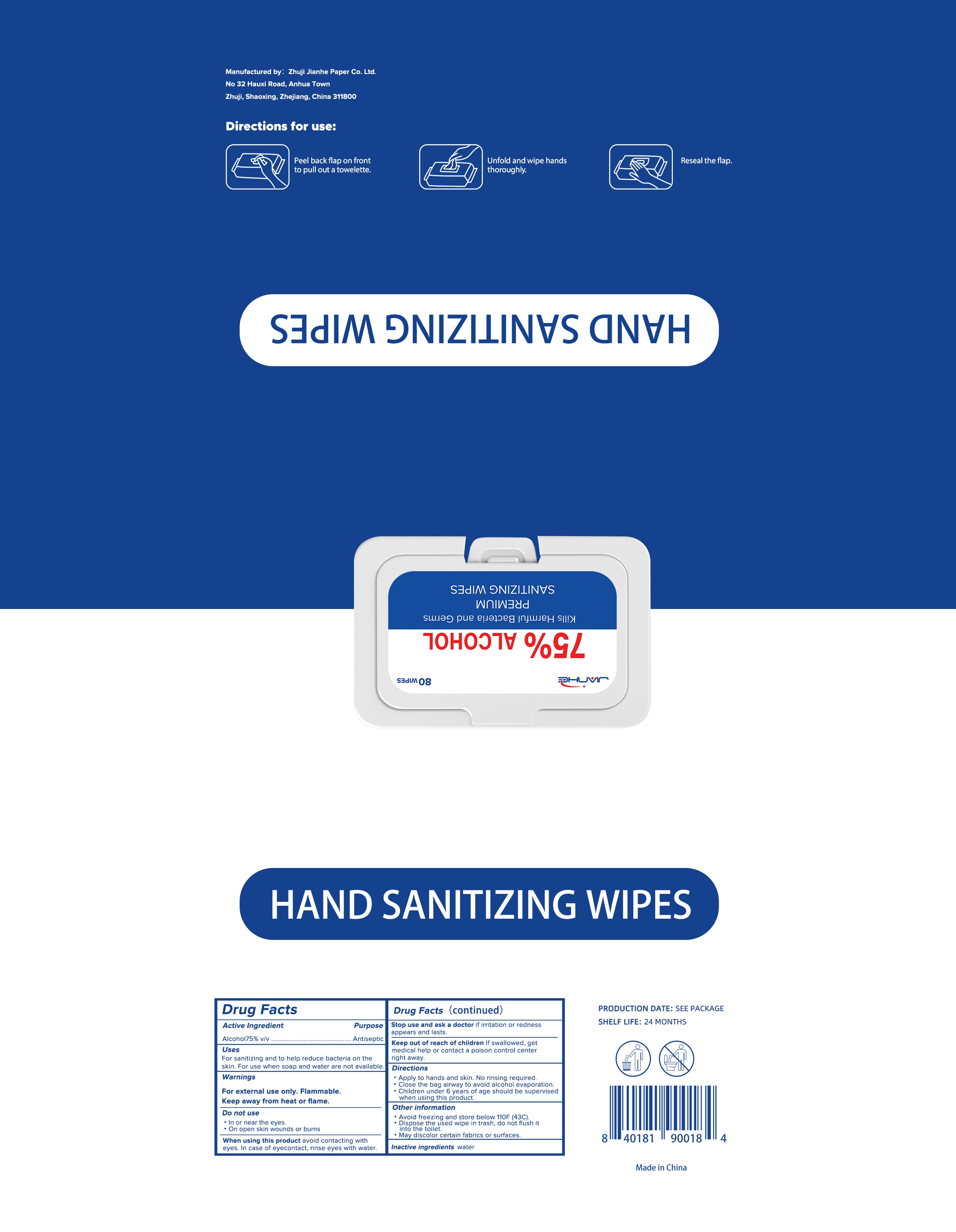 DRUG LABEL: ALCOHOL WIPES
NDC: 75163-006 | Form: CLOTH
Manufacturer: Zhuji Jianhe Paper Co., Ltd
Category: otc | Type: HUMAN OTC DRUG LABEL
Date: 20200920

ACTIVE INGREDIENTS: ALCOHOL 4 mL/1 1
INACTIVE INGREDIENTS: WATER

75163-006 50 CLOTH 80 CLOTH JIANHE 20200920

Active Ingredient(s)

Alcohol 75% v/v. Purpose: Antiseptic

Purpose

Antiseptic, HAND SANITIZING WIPES

Use

For sanitizing and to help reduce bacteria on the skin. For use when soap and water are not available.

Warnings

For external use only. Flammable. Keep away from heat or flame

Do not use

- In or near the eyes.
- On open skin wounds or burns.

When using this product avoid contacting with eyes. In case of eyecontatct, rinse eyes with water.

Stop use and ask a doctor if irritation or redness appears and lasts.

Keep out of reach of children. If swallowed, get medical help or contact a Poison Control Center right away.

Directions

- Apply to hands and skin. No rinsing required.
- Close the bag airway to avoid alcohol evaporation.
  - Children under 6 years of age should be supervised when using this product.
  - Directions for use: 1.Peel back flap on front to pull out a towelette. 2. Unfold and wipe hands thoroughly. 3. Reseal the flap.

Other information

- Avoid freezing and store below 110F (43C).
- Dispose the used wipe in trash, do not flush it into the toilet.
- May discolor certain fabrics or surfaces.

Inactive ingredients

Water

Package Label - Principal Display Panel

50 cloth in 1 BAG NDC: 75163-006-01

80 cloth in 1 BAG NDC: 75163-006-01